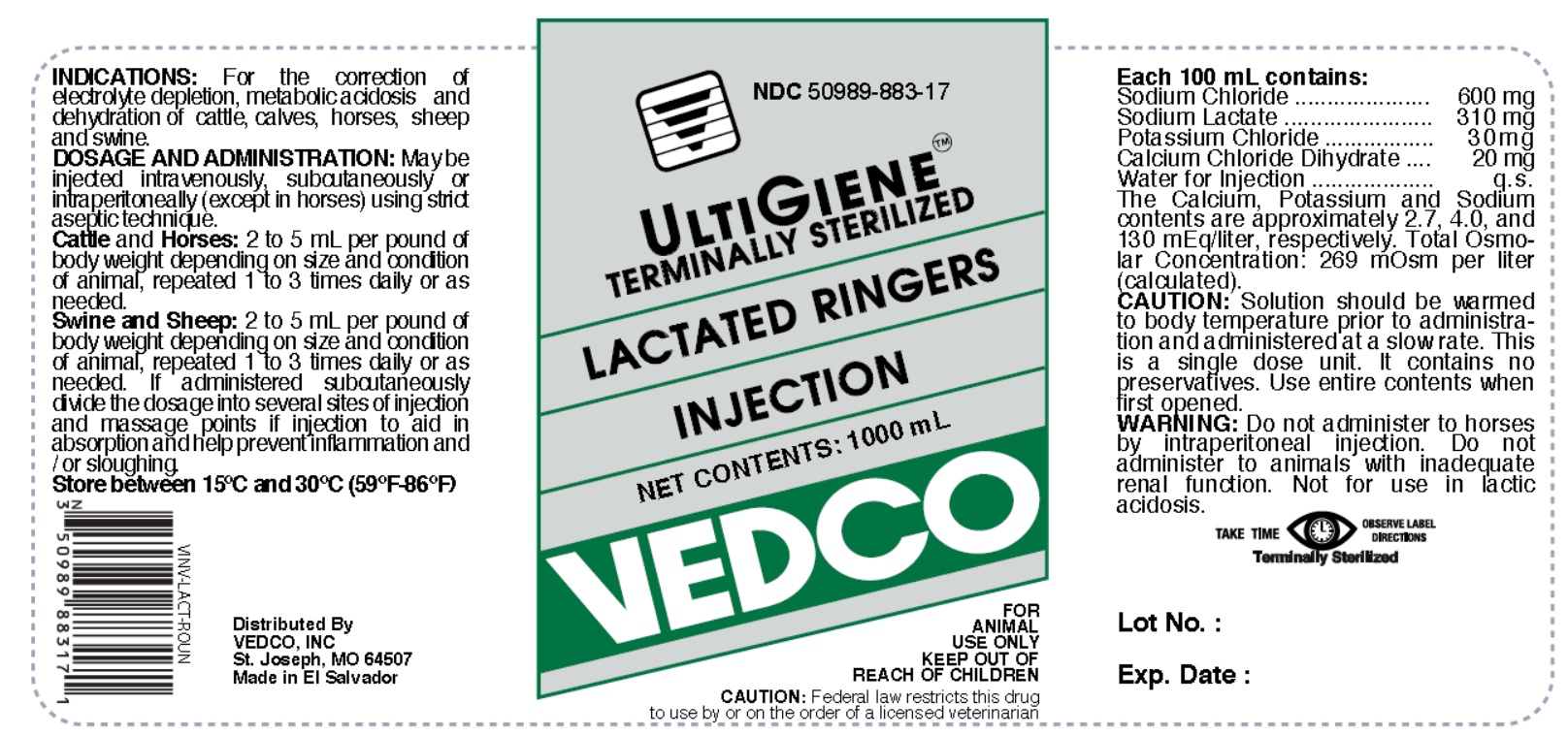 DRUG LABEL: Lactated Ringers
NDC: 50989-883 | Form: INJECTION, SOLUTION
Manufacturer: Vedco
Category: animal | Type: PRESCRIPTION ANIMAL DRUG LABEL
Date: 20190312

ACTIVE INGREDIENTS: SODIUM CHLORIDE 600 mg/100 mL; SODIUM LACTATE 310 mg/100 mL; POTASSIUM CHLORIDE 30 mg/100 mL; CALCIUM CHLORIDE 20 mg/100 mL

LACTATED RINGERS INJECTION

LACTATED RINGERS- lactated ringers injection, solution

Vedco

Disclaimer: This drug has not been found by FDA to be safe and effective, and this labeling has not been approved by FDA.

LACTATED RINGERS INJECTION

ACTIVE INGREDIENTS

Each 100 mL contains:

Sodium Chloride ....................... 600 mg
Sodium Lactate ........................ 310 mg
Potassium Chloride .................... 30 mg
Calcium Chloride Dihydrate ......... 20 mg
Water for Injection ........................ q.s.

The Calcium, Potassium and Sodium contents are approximately 2.7, 4.0, and 130 mEq/liter, respectively. Total Osmolar Concentration: 269 mOsm per liter (calculated).

INDICATIONS

For the correction of electrolyte depletion, metabolic acidosis and dehydration of cattle, calves, horses, sheep and swine.

DOSAGE AND ADMINISTRATION:

May be injected intravenously, subcutaneously or intraperitoneally (except in horses) using strict aseptic technique.

Cattle and Horses: 2 to 5 mL per pound of body weight depending on size and condition of animal, repeated 1 to 3 times daily or as needed.

Swine and Sheep: 2 to 5 mL per pound of body weight depending on size and condition of animal, repeated 1 to 3 times daily or as needed.

If administered subcutaneously divide the dosage into several sites of injection and massage points of injection to aid in absorption and help prevent inflammation and / or sloughing.

STORAGE

Store between 15°C and 30°C (59°F-86°F)

VETERINARY INDICATIONS

FOR ANIMAL USE ONLY

WARNING

KEEP OUT OFREACH OF CHILDREN

TAKE TIME OBSERVE LABEL DIRECTIONS

CAUTION:

Federal law restricts this drug to use by or on the order of a licensed veterinarian.

CAUTION:

Solution should be warmed to body temperature prior to administration and administered at a slow rate. This is a single dose unit. It contains no preservatives. Use entire contents when first opened.

WARNING:

Do not administer to horses by intraperitoneal injection. Do not administer to animals with inadequate renal function. Not for use in lactic acidosis.

INFORMATION FOR OWNERS/CAREGIVERS

Distributed By

VEDCO, INC.
St. Joseph, MO 64507

Made in El Salvador

STERILE NONPYROGENIC SOLUTION
CONTENTS | NDC | VINV #
1000 mL | 50989-883-17 | VINV-LACT-ROUN

PRINCIPAL DISPLAY PANEL

NDC 50989-883-17

ULTIGIENE

TERMINALLY STERILIZED

LACTATED RINGERS INJECTION

NET CONTENTS: 1000 mL

VEDCO

FOR ANIMAL USE ONLY

KEEP OUT OF REACH OF CHILDREN

CAUTION: Federal law restricts this drug to use by or on the order of licensed veterinarian